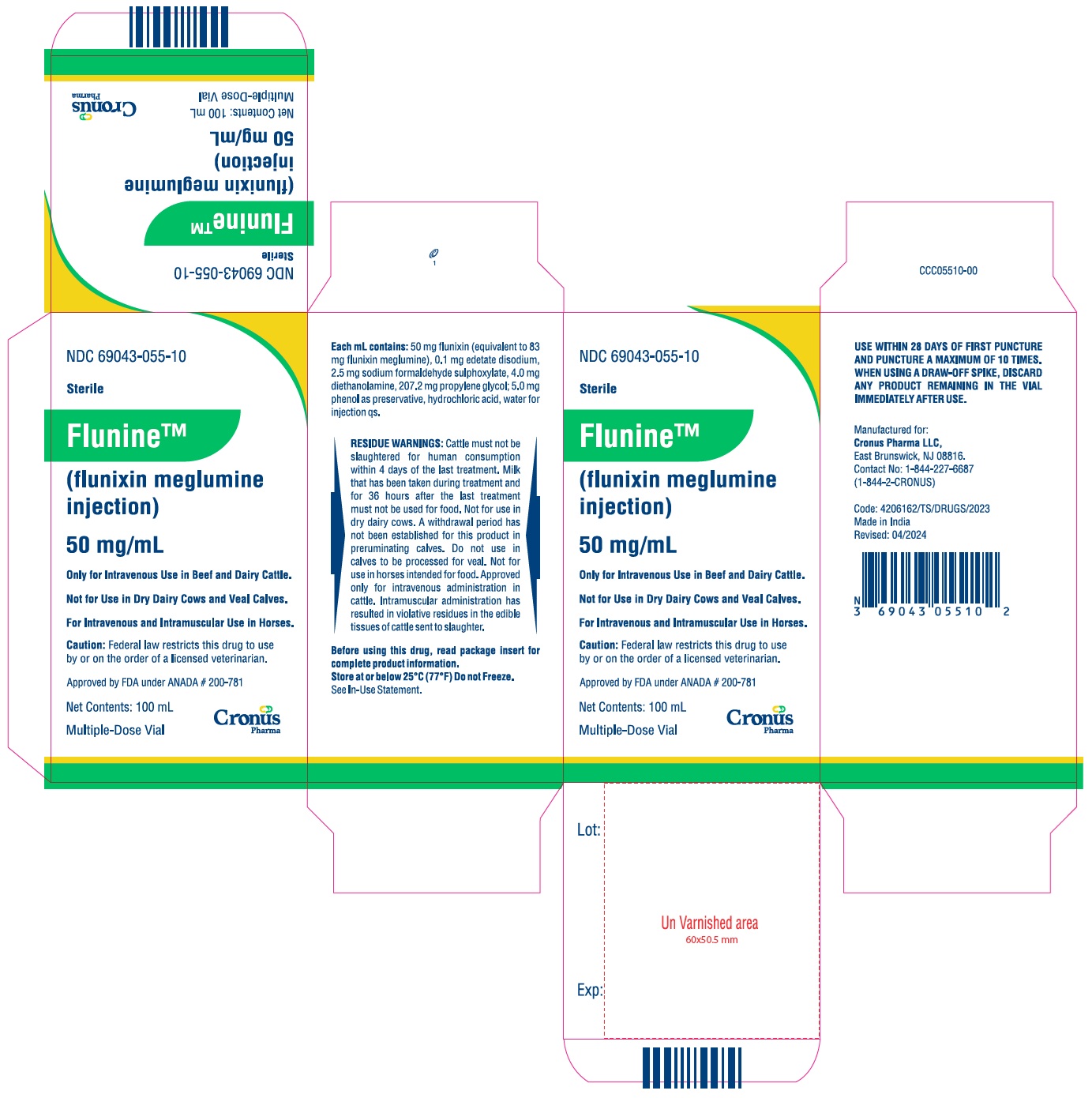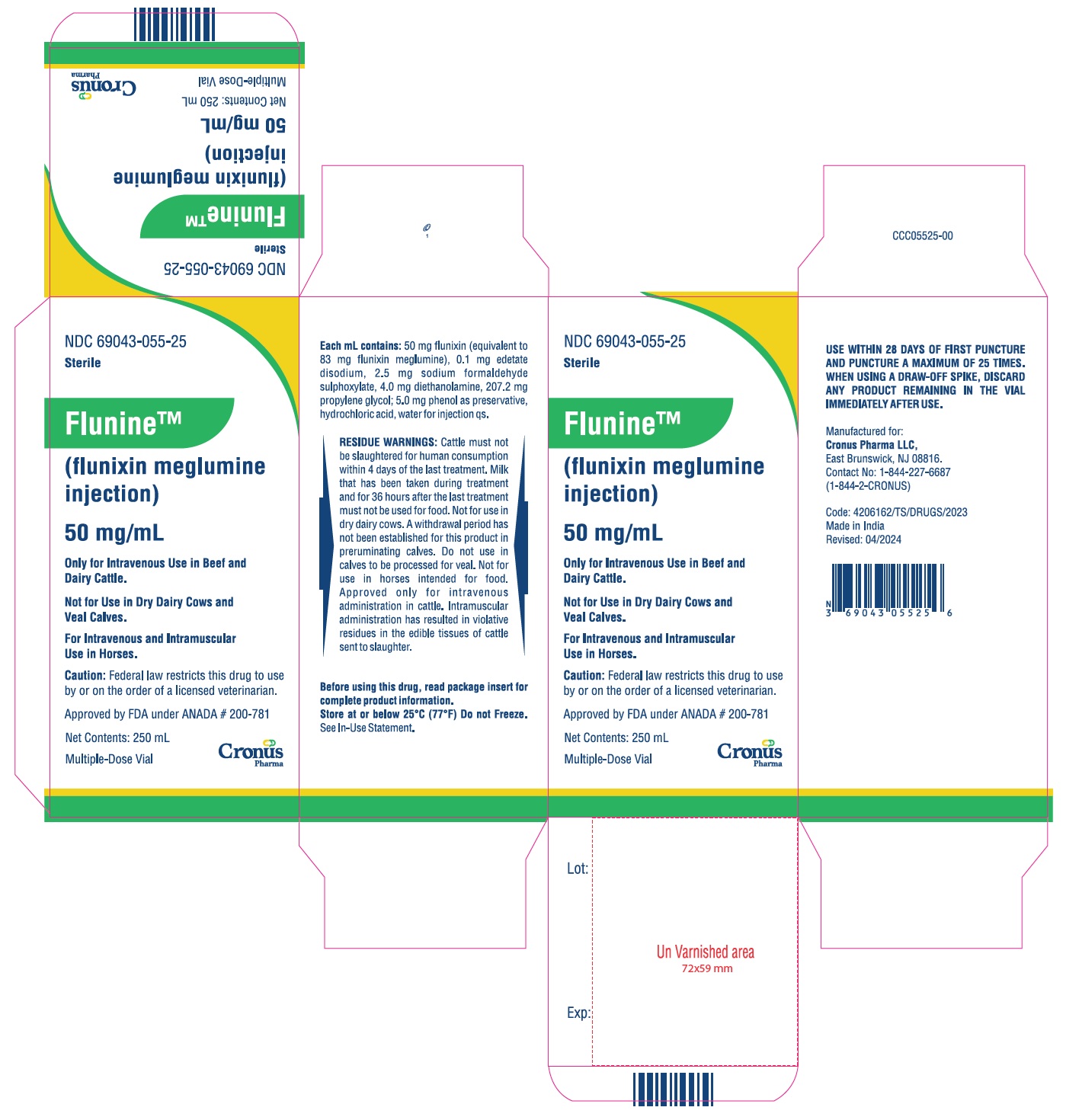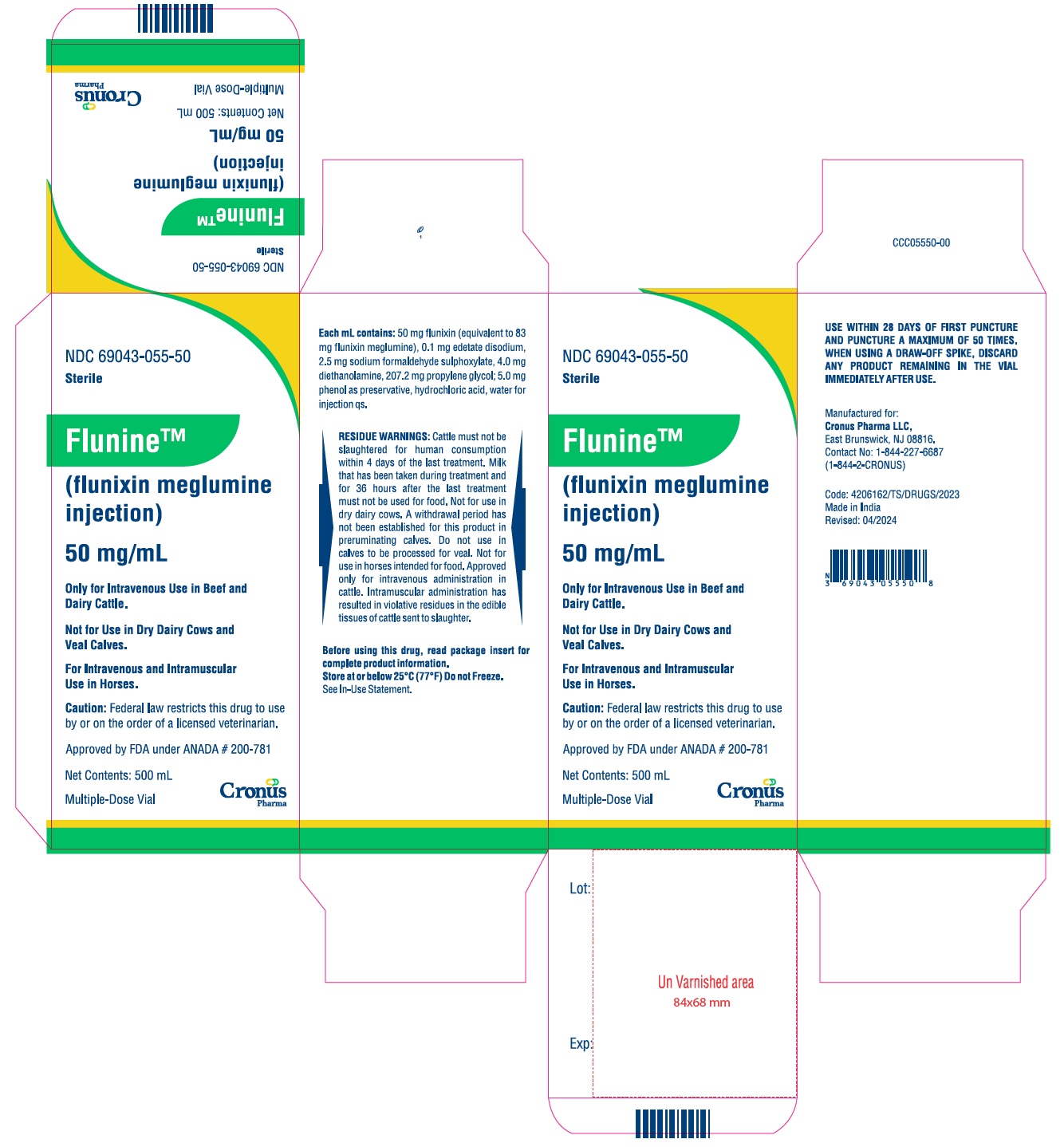 DRUG LABEL: Flunine
NDC: 69043-055 | Form: INJECTION
Manufacturer: Cronus Pharma LLC
Category: animal | Type: PRESCRIPTION ANIMAL DRUG LABEL
Date: 20250104

ACTIVE INGREDIENTS: FLUNIXIN MEGLUMINE 50 mg/1 mL

PRODUCT INFORMATION

Approved by FDA under ANADA # 200-781

FlunineTM (flunixin meglumine injection) 50 mg/mL

Only for Intravenous Use in Beef and Dairy Cattle.
Not for Use in Dry Dairy Cows and Veal Calves.
For Intravenous and Intramuscular Use in Horses.

CAUTION: Federal law restricts this drug to use by or on the order of a licensed veterinarian.

DESCRIPTION

Each milliliter of FlunineTM (flunixin meglumine injection) contains 50 mg flunixin (equivalent to 83 mg flunixin meglumine), 0.1 mg edetate disodium, 2.5 mg sodium formaldehyde sulfoxylate, 4.0 mg diethanolamine, 207.2 mg propylene glycol; 5.0 mg phenol as preservative, hydrochloric acid, water for injection qs.

PHARMACOLOGY

Flunixin meglumine is a potent, non-narcotic, nonsteroidal, analgesic agent with anti-inflammatory and antipyretic activity. It is significantly more potent than pentazocine, meperidine, and codeine as an analgesic in the rat yeast paw test.

Horse: Flunixin is four times as potent on a mg-per-mg basis as phenylbutazone as measured by the reduction in lameness and swelling in the horse. Plasma half-life in horse serum is 1.6 hours following a single dose of 1.1 mg/kg. Measurable amounts are detectable in horse plasma at 8 hours postinjection.

Cattle: Flunixin meglumine is a weak acid (pKa=5.82)^1 which exhibits a high degree of plasma protein binding (approximately 99%).^2 However, free (unbound) drug appears to readily partition into body tissues (Vss predictions range from 297 to 782 mL/kg.^2-5 Total body water is approximately equal to 570 mL/kg).^6 In cattle, elimination occurs primarily through biliary excretion.^7 This may, at least in part, explain the presence of multiple peaks in the blood concentration/time profile following IV administration.^2

In healthy cattle, total body clearance has been reported to range from 90 to 151 mL/kg/hr.^2-5 These studies also report a large discrepancy between the volume of distribution at steady state (VSS) and the volume of distribution associated with the terminal elimination phase (Vβ). This discrepancy appears to be attributable to extended drug elimination from a deep compartment.^8 The terminal half-life has been shown to vary from 3.14 to 8.12 hours.^2-5

Flunixin persists in inflammatory tissues^9 and is associated with anti-inflammatory properties which extend well beyond the period associated with detectable plasma drug concentrations.^4,9 These observations account for the counterclockwise hysteresis associated with flunixin's pharmacokinetic/pharmacodynamic relationships.^10

Therefore, prediction of drug concentrations based upon the estimated plasma terminal elimination half-life will likely underestimate both the duration of drug action and the concentration of drug remaining at the site of activity.

INDICATIONS

Horse: FlunineTM (flunixin meglumine injection) is recommended for the alleviation of inflammation and pain associated with musculoskeletal disorders in the horse. It is also recommended for the alleviation of visceral pain associated with colic in the horse.

Cattle: FlunineTM (flunixin meglumine injection) is indicated for the control of pyrexia associated with bovine respiratory disease, endotoxemia and acute bovine mastitis. FlunineTM is also indicated for the control of inflammation in endotoxemia.

DOSE AND ADMINISTRATION

USE WITHIN 28 DAYS OF FIRST PUNCTURE AND PUNCTURE A MAXIMUM OF 10 TIMES FOR 100 ML FILL, 25 TIMES FOR 250 ML FILL AND 50 TIMES FOR 500 ML FILL. WHEN USING A DRAW-OFF SPIKE, DISCARD ANY PRODUCT REMAINING IN THE VIAL IMMEDIATELY AFTER USE.

Horse: The recommended dose for musculoskeletal disorders is 0.5 mg per pound (1 mL/100 lbs) of body weight once daily. Treatment may be given by intravenous or intramuscular injection and repeated for up to 5 days. Studies show onset of activity is within 2 hours. Peak response occurs between 12 and 16 hours and duration of activity is 24-36 hours.

The recommended dose for the alleviation of pain associated with equine colic is 0.5 mg per pound of body weight. Intravenous administration is recommended for prompt relief. Clinical studies show pain is alleviated in less than 15 minutes in many cases. Treatment may be repeated when signs of colic recur. During clinical studies approximately 10% of the horses required one or two additional treatments. The cause of colic should be determined and treated with concomitant therapy.

Cattle: The recommended dose for control of pyrexia associated with bovine respiratory disease and endotoxemia and control of inflammation in endotoxemia, is 1.1 to 2.2 mg/kg (0.5 to 1 mg/lb; 1 to 2 mL per 100 lbs) of body weight given by slow intravenous administration either once a day as a single dose or divided into two doses administered at 12-hour intervals for up to 3 days. The total daily dose should not exceed 2.2 mg/kg (1.0 mg/lb) of body weight. Avoid rapid intravenous administration of the drug.

The recommended dose for acute bovine mastitis is 2.2 mg/kg (1 mg/lb; 2 ml per 100 lbs) of body weight given once by intravenous administration.

CONTRAINDICATIONS

Horse: There are no known contraindications to this drug when used as directed. Intra-arterial injection should be avoided. Horses inadvertently injected intra-arterially can show adverse reactions. Signs can be ataxia, incoordination, hyperventilation, hysteria, and muscle weakness. Signs are transient and disappear without antidotal medication within a few minutes. Do not use in horses showing hypersensitivity to flunixin meglumine.

Cattle: NSAIDs inhibit production of prostaglandins which are important in signaling the initiation of parturition. The use of flunixin can delay parturition and prolong labor which may increase the risk of stillbirth. Do not use FlunineTM (flunixin meglumine injection) within 48 hours of expected parturition. Do not use in animals showing hypersensitivity to flunixin meglumine. Use judiciously when renal impairment or gastric ulceration are suspected.

RESIDUE WARNING

RESIDUE WARNINGS: Cattle must not be slaughtered for human consumption within 4 days of the last treatment. Milk that has been taken during treatment and for 36 hours after the last treatment must not be used for food. Not for use in dry dairy cows. A withdrawal period has not been established for this product in preruminating calves. Do not use in calves to be processed for veal. Not for use in horses intended for food. Approved only for intravenous administration in cattle. Intramuscular administration has resulted in violative residues in the edible tissues of cattle sent to slaughter.

PRECAUTIONS

As a class, cyclo-oxygenase inhibitory NSAIDs may be associated with gastrointestinal and renal toxicity. Sensitivity to drug-associated adverse effects varies with the individual patient. Patients at greatest risk for renal toxicity are those that are dehydrated, on concomitant diuretic therapy, or those with renal, cardiovascular, and/or hepatic dysfunction.

Since many NSAIDs possess the potential to induce gastrointestinal ulceration, concomitant use of FlunineTM (flunixin meglumine injection) with other anti-inflammatory drugs, such as other NSAIDs and corticosteroids, should be avoided or closely monitored.

Horse: The effect of FlunineTM (flunixin meglumine injection) on pregnancy has not been determined. Studies to determine activity of FlunineTM when administered concomitantly with other drugs have not been conducted. Drug compatibility should be monitored closely in patients requiring adjunctive therapy.

Cattle: Do not use in bulls intended for breeding, as reproductive effects of FlunineTM (flunixin meglumine injection) in these classes of cattle have not been investigated. NSAIDs are known to have potential effects on both parturition (See Contraindications) and the estrous cycle. There may be a delay in the onset of estrus if flunixin is administered during the prostaglandin phase of the estrous cycle. NSAIDs are known to have the potential to delay parturition through a tocolytic effect. The use of NSAIDs in the immediate post-partum period may interfere with uterine involution and expulsion of fetal membranes. Cows should be monitored carefully for placental retention and metritis if FlunineTM is used within 24 hours after parturition.

SAFETY

Horse: A 3-fold intramuscular dose of 1.5 mg/lb of body weight daily for 10 consecutive days was safe.

No changes were observed in hematology, serum chemistry, or urinalysis values. Intravenous dosages of 0.5 mg/lb daily for 15 days; 1.5 mg/lb daily for 10 days; and 2.5 mg/lb daily for 5 days produced no changes in blood or urine parameters. No injection site irritation was observed following intramuscular injection of the 0.5 mg/lb recommended dose. Some irritation was observed following a 3-fold dose administered intramuscularly.

Cattle: No flunixin-related changes (adverse reactions) were noted in cattle administered a 1x (2.2 mg/kg; 1.0 mg/lb) dose for 9 days (three times the maximum clinical duration). Minimal toxicity manifested itself at moderately elevated doses (3x and 5x) when flunixin was administered daily for 9 days, with occasional findings of blood in the feces and/or urine. Discontinue use if hematuria or fecal blood are observed.

ADVERSE REACTIONS

In horses, isolated reports of local reactions following intramuscular injection, particularly in the neck, have been received. These include localized swelling, sweating, induration, and stiffness. In rare instances in horses, fatal or nonfatal clostridial infections or other infections have been reported in association with intramuscular use of flunixin meglumine injection. In horses and cattle, rare instances of anaphylactic-like reactions, some of which have been fatal, have been reported, primarily following intravenous use.

HOW SUPPLIED

FlunineTM (flunixin meglumine injection), 50 mg/ mL, is available in 100-mL (NDC 69043-055-10), 250-mL (NDC 69043-055-25) and 500-mL (NDC 69043-055-50) multi-dose vials.

STORAGE AND HANDLING

Store at or below 25°C (77°F) Do not Freeze. See the in-use directions provided in the DOSE AND ADMINISTRATION section.

REFERENCES

1. Johansson M, Anler EL. Gas chromatographic analysis of flunixin in equine urine after extractive methylation. J Chromatogr. 1988; 427:55-66.

2. Odensvik K, Johansson M. High-performance liquid chromatography method for determination of flunixin in bovine plasma and pharmacokinetics after single and repeated doses of the drug. Am J Vet Res. 1995; 56:489-495.

3. Anderson KL, Neff-Davis CA, Davis LE, Bass VD. Pharmacokinetics of flunixin meglumine in lactating cattle after single and multiple intramuscular and intravenous administrations. Am J Vet Res. 1990; 51:1464-1467.

4. Odensvik K. Pharmacokinetics of flunixin and its effect on prostaglandin F2α metabolite concentrations after oral and intravenous administration in heifers. J Vet Pharmacol Ther. 1995; 18:254-259.

5. Hardee GE, Smith JA, Harris SJ. Pharmacokinetics of flunixin meglumine in the cow. Res Vet Sci. 1985; 39:110-112.

6. Ruckebusch Y, Phaneuf LP, Dunlop R. Physiology of Small and Large Animals. Chapter 2: “Body Fluid Compartments,” Philadelphia, Pa: B.C. Decker; 1991:8-18.

7. Kopcha M, Ahl AS. Experimental uses of flunixin meglumine and phenylbutazone in food-producing animals. J Am Vet Med Assoc. 1989; 194:45-49.

8. Wagner JG. Significance of ratios of different volumes of distribution in pharmacokinetics. Biopharm & Drug Dispos. 1983; 4:263-270.

9. Lees P, Higgins AJ. Flunixin inhibits prostaglandin E2 production in equine inflammation. Res Vet Sci. 1984; 37:347-349.

10. Landoni MF, Cunningham FM, Lees P. Determination of pharmacokinetics and pharmacodynamics of flunixin in calves by use of pharmacokinetic/pharmacodynamic modeling. Am J Vet Res. 1995; 56:786-794.

Manufactured for:
Cronus Pharma LLC,
East Brunswick, NJ 08816.
Contact No: 1-844-227-6687
(1-844-2-CRONUS)

Made in India

April 2024

PACKAGE LABEL.PRINCIPAL DISPLAY PANEL

NDC 69043-055-10

Sterile

FlunineTM
(flunixin meglumine injection)

50 mg/mL

Only for Intravenous Use in Beef and Dairy Cattle.
Not for Use in Dry Dairy Cows and Veal Calves.
For Intravenous and Intramuscular Use in Horses.

CAUTION: Federal law restricts this drug to use by or on the order of a licensed veterinarian.

Approved by FDA under ANADA # 200-781

Net contents: 100 mL

Multiple-Dose Vial

PACKAGE LABEL.PRINCIPAL DISPLAY PANEL

NDC 69043-055-25

Sterile

FlunineTM
(flunixin meglumine injection)

50 mg/mL

Only for Intravenous Use in Beef and Dairy Cattle.
Not for Use in Dry Dairy Cows and Veal Calves.
For Intravenous and Intramuscular Use in Horses.

CAUTION: Federal law restricts this drug to use by or on the order of a licensed veterinarian.

Approved by FDA under ANADA # 200-781

Net contents: 250 mL

Multiple-Dose Vial

PACKAGE LABEL.PRINCIPAL DISPLAY PANEL

NDC 69043-055-50

Sterile

FlunineTM
(flunixin meglumine injection)

50 mg/mL

Only for Intravenous Use in Beef and Dairy Cattle.
Not for Use in Dry Dairy Cows and Veal Calves.
For Intravenous and Intramuscular Use in Horses.

CAUTION: Federal law restricts this drug to use by or on the order of a licensed veterinarian.

Approved by FDA under ANADA # 200-781

Net contents: 500 mL

Multiple-Dose Vial